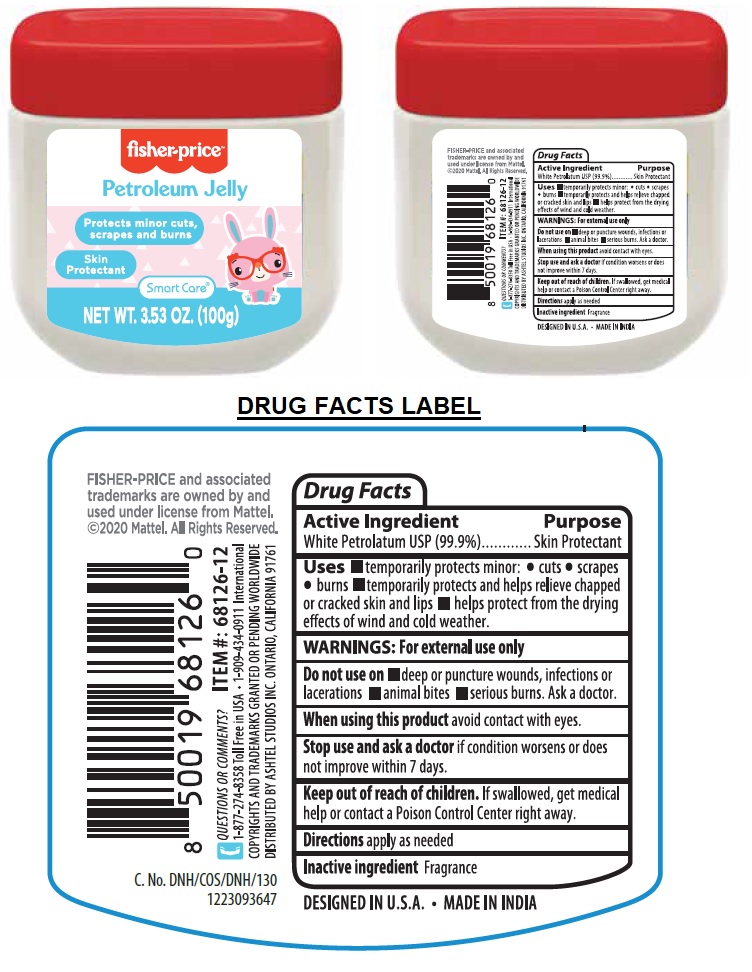 DRUG LABEL: Fisher-Price Petroleum Jelly
NDC: 70108-068 | Form: JELLY
Manufacturer: Ashtel Studios, Inc
Category: otc | Type: HUMAN OTC DRUG LABEL
Date: 20221229

ACTIVE INGREDIENTS: PETROLATUM 99.9 g/100 g

Fisher-price™ Petroleum Jelly

Active Ingredient

White Petrolatum USP (99.9%)

Purpose

Skin Protectant

INDICATIONS AND USAGE

Uses ■ temporarily protects minor: • cuts • scrapes • burns ■ temporarily protects and helps relieve chapped or cracked skin and lips ■ helps protect from the drying effects of wind and cold weather.

WARNINGS: For external use only

Do not use on ■ deep or puncture wounds, infections or lacerations ■ animal bites ■ serious burns. Ask a doctor.

When using this product avoid contact with eyes.

Stop use and ask a doctor if condition worsens or does not improve within 7 days.

Keep out of reach of children. If swallowed, get medical help or contact a Poison Control Center right away.

DOSAGE AND ADMINISTRATION

Directions apply as needed

Inactive ingredient Fragrance

Protects minor cuts, scrapes and burns

Skin Protectant

Smart Care®

FISHER-PRICE and associated trademarks are owned by and used under license from Mattel. ©2020 Mattel. All Rights Reserved.

QUESTIONS OR COMMENTS?

1-877-274-8358 Toll Free in USA • 1-909-434-0911 International

COPYRIGHTS AND TRADEMARKS GRANTED OR PENDING WORLDWIDE

DISTRIBUTED BY ASHTEL STUDIOS INC. ONTARIO, CALIFORNIA 91761

DESIGNED IN U.S.A. • MADE IN INDIA